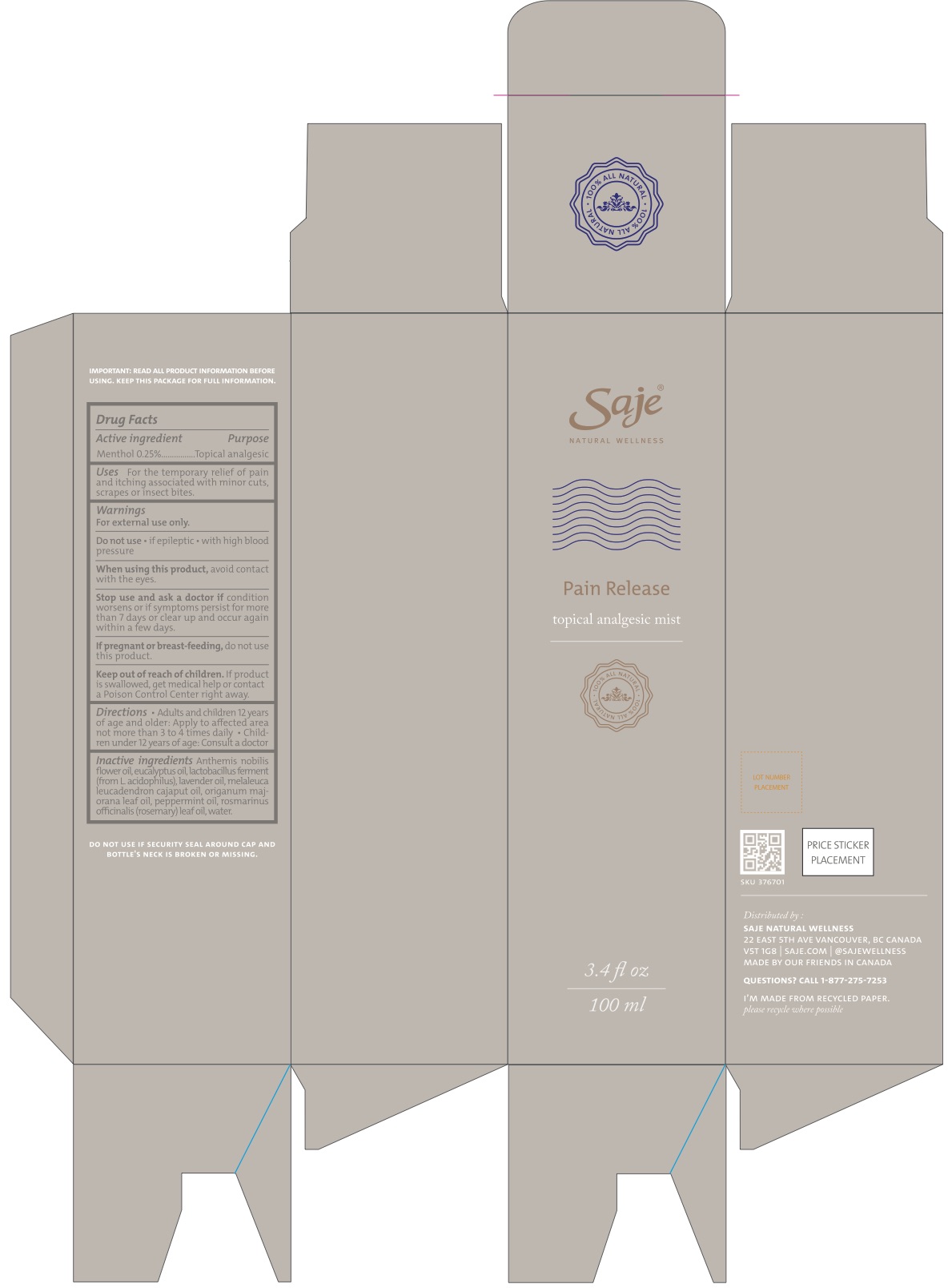 DRUG LABEL: Pain Release
NDC: 70983-005 | Form: LIQUID
Manufacturer: Saje Natural Business Inc.
Category: otc | Type: HUMAN OTC DRUG LABEL
Date: 20260113

ACTIVE INGREDIENTS: MENTHOL 2.23 mg/1 mL
INACTIVE INGREDIENTS: CHAMAEMELUM NOBILE FLOWER OIL; EUCALYPTUS OIL; LAVENDER OIL; CAJUPUT OIL; SWEET MARJORAM OIL; PEPPERMINT OIL; ROSEMARY OIL; WATER

Pain Release Topical Analgesic Mist (100 ml)

DRUG FACTS Active ingredient

Menthol 0.25%

Purpose Topical Analgesic

Uses For the temporary relief of pain and itching associated with minor cuts, scrapes, or insect bites.

Warnings

For external use only.

Do not use

- if epileptic
- with high blood pressure

When using this product,

avoid contact with the eyes

Stop use and ask a doctor if

condition worsens, or if symptoms persist for more than 7 days or clear up and occur again within a few days.

If pregnant or breast-feeding,

do not use this product.

Keep out of reach of children.

If product is swallowed, get medical help or contact a Poison Control Center right away.

Directions

- Adults and children 12 years of age and older: Apply to affected area

DOSAGE AND ADMINISTRATION

not more than 3 to 4 times daily.

- Not recommended for children under 12 years of age.

Inactive ingredients

Anthemis nobilis flower oil, eucalyptus oil, lavender oil, melaleuca leucadendron cajaput oil, origanum majorana leaf oil, peppermint oil, rosmarinus officinalis (rosemary) leaf oil, and water.

Questions?

1-877-275-7253

Distributed by: SAJE NATURAL WELLNESS 22 East 5th Ave Vancouver, BC Canada V5T 1G8 | saje.com | 1-877-275-7253 | Made by our friends in Canada

DO NOT USE IF SECURITY SEAL AROUND CAP AND BOTTLE'S NECK IS BROKEN OR MISSING

SKU 376701

DISPOSAL AND WASTE HANDLING

We support recycling. Please recycle where possible.

Pain Release Topical Analgesic Mist (100 ml)

Saje® Natural Wellness

Pain Release

Topical Analgesic Mist

3.4 fl. oz. | 100 ml